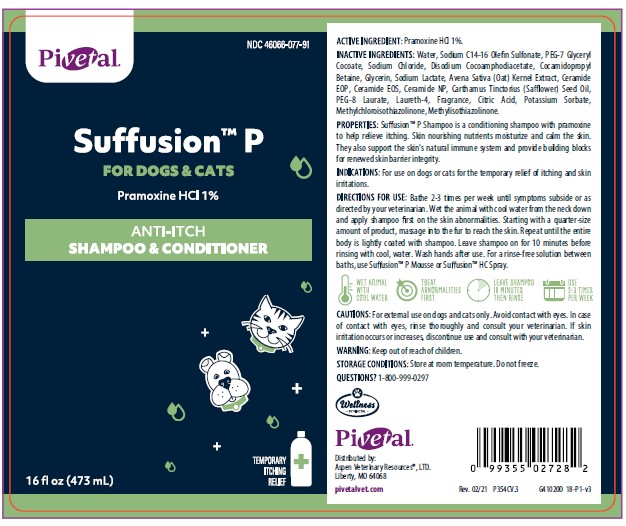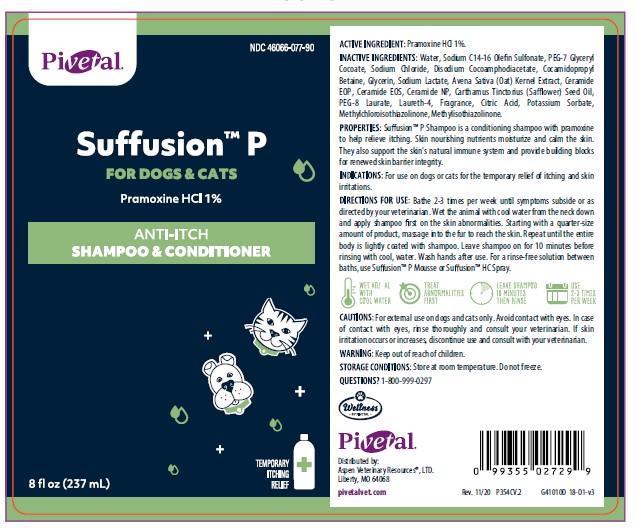 DRUG LABEL: Suffusion
NDC: 46066-077 | Form: SHAMPOO
Manufacturer: Aspen Veterinary Resource, LTD.
Category: animal | Type: OTC ANIMAL DRUG LABEL
Date: 20210402

ACTIVE INGREDIENTS: PRAMOXINE HYDROCHLORIDE 10 mg/1 mL
INACTIVE INGREDIENTS: WATER; SODIUM C14-16 OLEFIN SULFONATE; PEG-7 GLYCERYL COCOATE; SODIUM CHLORIDE; DISODIUM COCOAMPHODIACETATE; COCAMIDOPROPYL BETAINE; GLYCERIN; SODIUM LACTATE; AVENANTHRAMIDES; CERAMIDE 1; CERAMIDE EOS; CERAMIDE NP; SAFFLOWER OIL; PEG-8 LAURATE; LAURETH-4; CITRIC ACID MONOHYDRATE; POTASSIUM SORBATE; METHYLCHLOROISOTHIAZOLINONE; METHYLISOTHIAZOLINONE

DESCRIPTION

Suffusion™ P

FOR DOGS AND CATS

Pramoxine HCl 1%

ANTI-ITCH

SHAMPOO & CONDITIONER

ACTIVE INGREDIENTS: Pramoxine HCI 1%.

INACTIVE INGREDIENTS: Water, Sodium C14-16 Olefin Sulfonate, PEG-7 Glyceryl Cocoate, Sodium Chloride, Disodium Cocoamphodiacetate, Cocamidopropyl Betaine, Glycerin, Sodium Lactate, Avena Sativa (Oat) Kernal Extract, Ceramide EOP, Ceramide EOS, Ceramide NP, Carthamus Tinctorius (Safflower) Seed Oil, PEG-8, Laurate, Laureth-4, Fragrance, Citric Acid, Potassium Sorbate, Methylchloroisothiazolinone, Methylisothiazolinone.

PROPERTIES: Suffusion™ P Shampoo is a conditioning shampoo with pramoxine to help relieve itching. Skin nourishing nutrients moisturize and calm the skin. They also support the skin's natural immune system and provide building blocks for renewed skin barrier integrity.

INDICATIONS AND USAGE

INDICATIONS: For use on dogs or cats for the temporary relief of itching and skin irritations.

DIRECTIONS FOR USE: Bathe 2-3 times per week until symptoms subside or as directed by your veterinarian. Wet the animal with cool water from the neck down and apply shampoo first on the skin abnormalities. Starting with a quarter-size amount of product, massage into the fur to reach the skin. Repeat until the entire body is lightly coated with shampoo. Leave shampoo on for 10 minutes before rinsing with cool water. Wash hands after use. For a rinse-free solution between baths, use Suffusion™ P Mousse or Suffusion HC Spray.

WARNINGS AND PRECAUTIONS

CAUTIONS: For external use on dogs and cats only. Avoid contact with eyes. In case of contact with eyes, rinse thoroughly and consult your veterinarian. If skin irritation occurs or increases, discontinue use and consult with your veterinarian.

WARNING: Keep out of reach of children.

STORAGE AND HANDLING

STORAGE CONDITIONS: Store at room temperature. Do not freeze.

QUESTIONS? 1-800-999-0297

Pivetal

Distributed by:
Aspen Veterinary Resources , LTD.
Liberty, MO 64068
www.pivetalvet.com

PRINCIPAL DISPLAY PANEL - 8 OUNCE (237 mL) Bottle

Pivetal

NDC 46066-077-90

SUFFUSION™ P

FOR CATS & DOGS

Pramoxine HCl 1%

ANTI-ITCH

SHAMPOO & CONDITIONER

8 fl oz (237 mL)

PRINCIPAL DISPLAY PANEL - 16 OUNCE (473 mL) Bottle

Pivetal

NDC 46066-077-91

SUFFUSION™ P

FOR CATS & DOGS

Pramoxine HCl 1%

ANTI-ITCH

SHAMPOO & CONDITIONER

16 fl oz (473 mL)